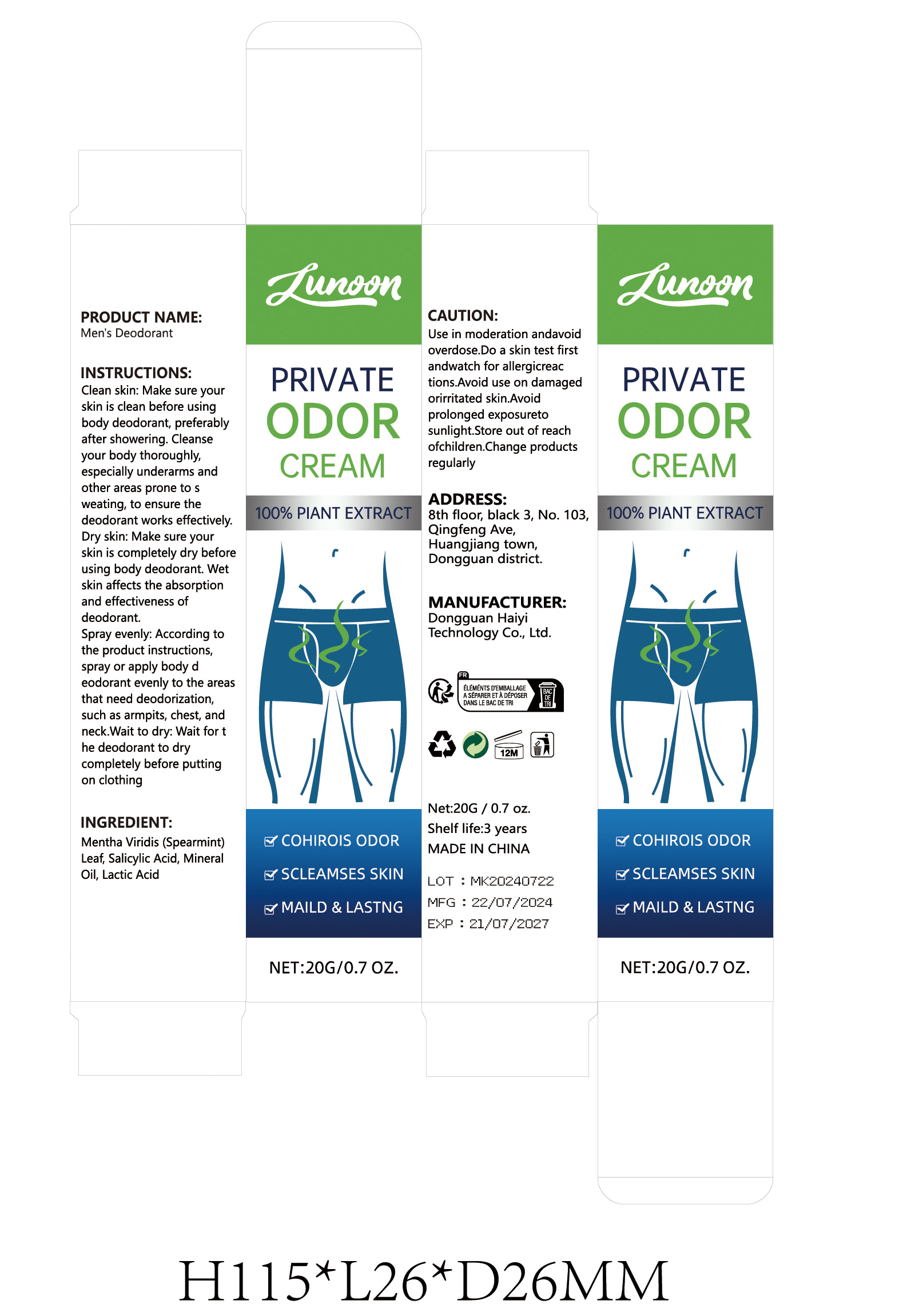 DRUG LABEL: Men s Deodorant
NDC: 84732-024 | Form: CREAM
Manufacturer: Dongguan Haiyi Technology Co.,Ltd.
Category: otc | Type: HUMAN OTC DRUG LABEL
Date: 20240928

ACTIVE INGREDIENTS: N-SALICYLOYLGLYCINE 1 mg/100 g; LACTIC ACID 1 mg/100 g
INACTIVE INGREDIENTS: SPEARMINT; MINERAL OIL

ACTIVE INGREDIENT

Salicylic Acid

Lactic Acid

Inactive ingredient

Mentha Viridis (Spearmint) Leaf

Mineral Oil

Purpose section

COHIROIS ODOR
SCLEAMSES SKIN
MAILD & LASTNG

Warning

Use in moderation and avoid overdose.Do a skin test first and watch for allergic reactions.Avoid use on damaged orirritated skin.Avoid prolonged exposure to sunlight.Store out of reach of children.Change products regularly

stop use

This product may cause allergic reactions in asmall number of people.
lf youexperience any discomfort,please stop using it immediately.

not use

Not suitable for use by children, pregnantor breast feeding people.

OUT OF CHILDREN

KEEP THE PRODUCT OUT OF REACH OF CHILDREN to

HOW TO USE

1.Clean skin: Make sure your skin is clean before using body deodorant, preferably after showering. Cleanse your body thoroughly,especially underarms and other areas prone to sweating, to ensure the deodorant works effectively.

2.Dry skin: Make sure your skin is completely dry beforeusing body deodorant. Wet skin affects the absorption and effectiveness of deodorant.
3.Spray evenly: According to the product instructions,spray or apply body deodorant evenly to the areas that need deodorization,such as armpits, chest, and neck.

4.Wait to dry: Wait for the deodorant to dry completely before puttingon clothing

Dosage

It is recommended to use it once before going out